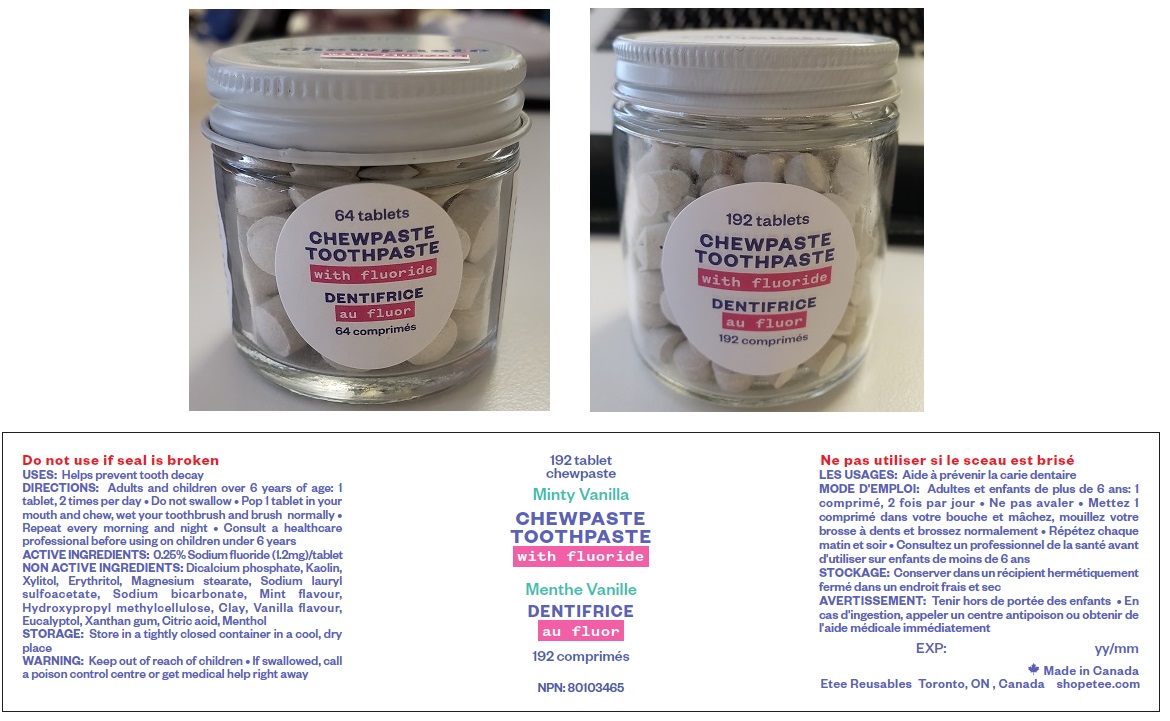 DRUG LABEL: Chewpaste with Fluoride
NDC: 81048-008 | Form: TABLET, CHEWABLE
Manufacturer: 2557807 Ontario Inc
Category: otc | Type: HUMAN OTC DRUG LABEL
Date: 20201117

ACTIVE INGREDIENTS: SODIUM FLUORIDE 1.2 mg/1 1
INACTIVE INGREDIENTS: ANHYDROUS DIBASIC CALCIUM PHOSPHATE; KAOLIN; XYLITOL; ERYTHRITOL; MAGNESIUM STEARATE; SODIUM LAURYL SULFOACETATE; SODIUM BICARBONATE; MINT; HYPROMELLOSE, UNSPECIFIED; BENTONITE; VANILLA BEAN; EUCALYPTOL; XANTHAN GUM; CITRIC ACID MONOHYDRATE; MENTHOL, UNSPECIFIED FORM

etee Chewpaste Toothpaste with Fluoride

ACTIVE INGREDIENTS:

0.25% Sodium fluoride (1.2mg)/tablet

PURPOSE:

Dentifrice

USES:

Helps prevent tooth decay

DIRECTIONS:

Adults and children over 6 years of age: 1 tablet, 2 times per day • Do not swallow • Pop 1 tablet in your mouth and chew, wet your toothbrush and brush normally • Repeat every morning and night • Consult a healthcare professional before using on children under 6 years

STORAGE:

Store in a tightly closed container in a cool, dry place

NON ACTIVE INGREDIENTS:

Dicalcium phosphate, Kaolin, Xylitol, Erythritol, Magnesium stearate, Sodium lauryl sulfoacetate, Sodium bicarbonate, Mint flavour, Hydroxypropyl methylcellulose, Clay, Vanilla flavour, Eucalyptol, Xanthan gum, Citric acid, Menthol

WARNING:

• If swallowed, call a poison control centre or get medical help right away

Keep out of reach of children

Minty Vanilla

Do not use if seal is broken

Made in Canada

Etee Reusables Toronto, ON, Canada, shopetee.com